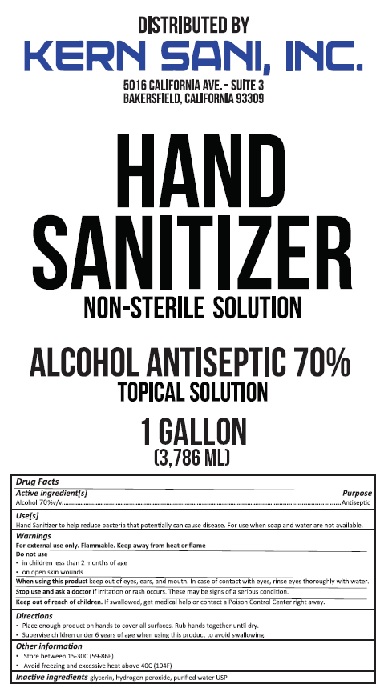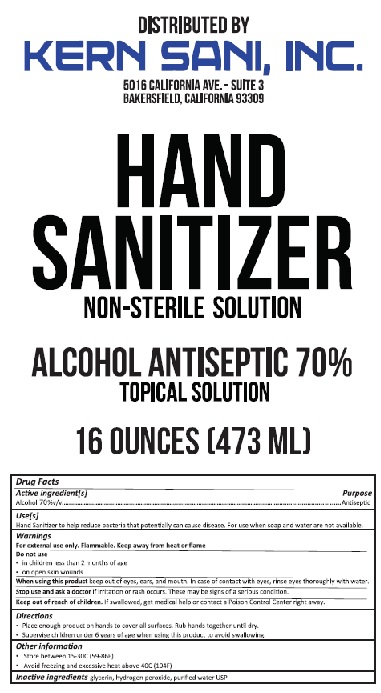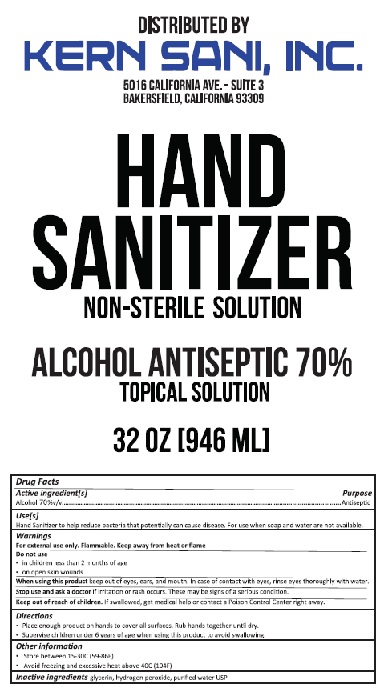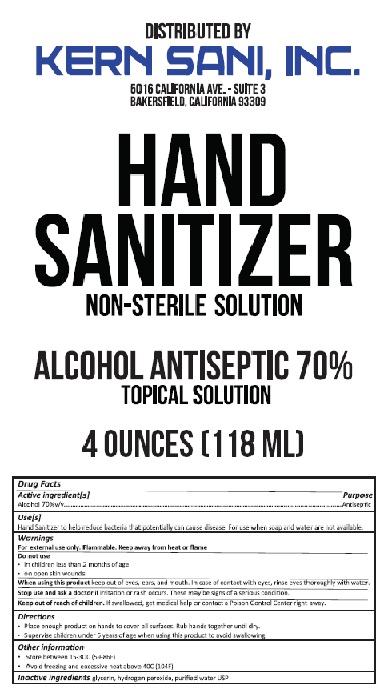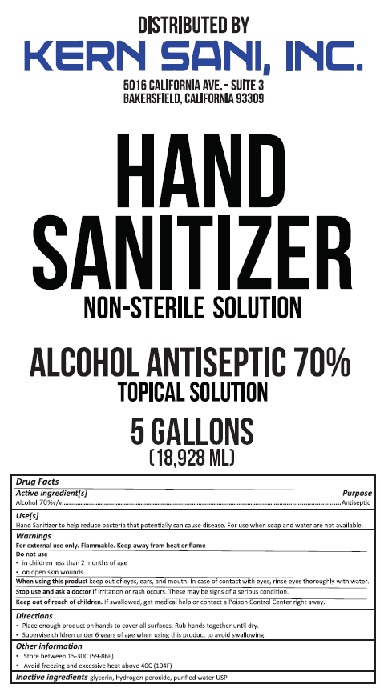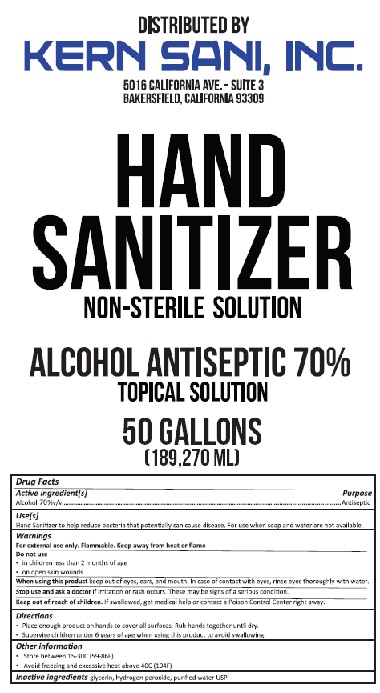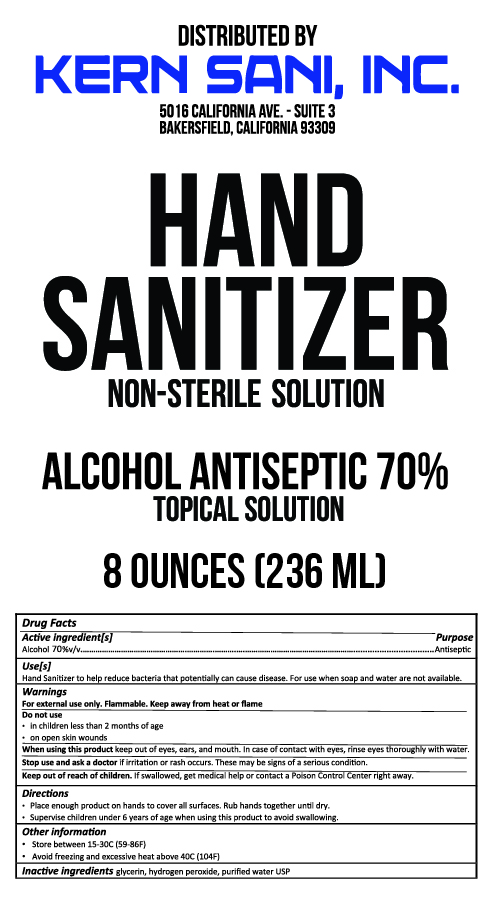 DRUG LABEL: Kern Sani Hand Sanitizer
NDC: 77804-001 | Form: SOLUTION
Manufacturer: KERN SANI, INC.
Category: otc | Type: HUMAN OTC DRUG LABEL
Date: 20211105

ACTIVE INGREDIENTS: ALCOHOL 70 mL/100 mL
INACTIVE INGREDIENTS: GLYCERIN; HYDROGEN PEROXIDE; WATER

Drug Facts

Active Ingredient[s]

Alcohol 70%

Purpose

Antiseptic

INDICATIONS AND USAGE

Use[s]

Hand Sanitizer to help reduce bacteria that potentially can cause disease. For use when soap and water are not available.

Warnings

For external use only. Flammable. Keep away from heat or flame

Do not use

- in children less than 2 months of age

- on open skin wounds

When using this product keep out of eyes, ears, and mouth. In case of contact with eyes, rinse eyes thoroughly with water.

Stop use and ask a doctor if irritation or rash occurs. These may be signs of a serious condition.

Keep out of reach of children. If swallowed, get medical help or contact a Poison Control Center right away.

Directions

- Place enough product on hands to cover all surfaces. Rub hands together until dry.

- Supervise children under 6 years of age when using this product to avoid swallowing.

Other information

- Store between 15-30C (59-86F)

- Avoid freezing and excessive heat above 40C (104F)

Inactive ingredients

glycerin, hydrogen peroxide, purified water USP

Principal Display Package

DISTRIBUTED BY

KERN SANI, INC.

5016 CALIFORNIA AVE. - SUITE 3

BAKERSFIELD, CA 93309

HAND SANITIZER

NON-STERILE SOLUTION

ALCOHOL ANTISEPTIC 70%

TOPICAL SOLUTION

4 OUNCES (118 ML)

8 OZ

16 OZ

32 OZ

1 Gal

5 Gal

50 Gal

res